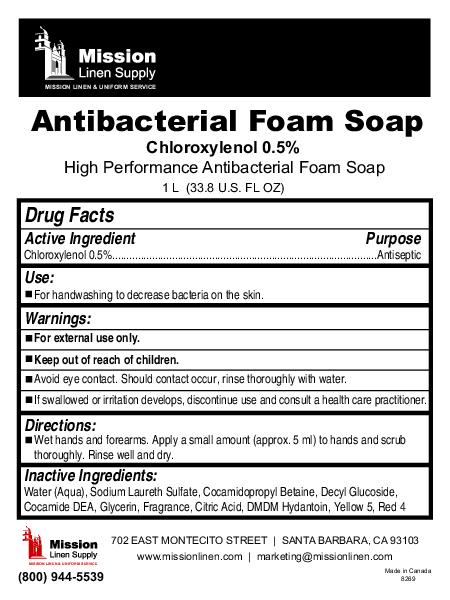 DRUG LABEL: Antibacterial Foam 
								
NDC: 51053-501 | Form: SOAP
Manufacturer: Sanihealth Products Corporation
Category: otc | Type: HUMAN OTC DRUG LABEL
Date: 20100518

ACTIVE INGREDIENTS: Chloroxylenol 5 mL/1000 mL

Antibacterial Foam

Warnings:
For external use only.

Keep out of reach of children.

Avoid eye contact. Should contact occur, rinse thoroughly with water.

If swallowed or irritation develops, discontinue use and consult a health care practitioner.

Inactive Ingredients:

Water (Aqua), Sodium Lareth Sulfate, Cocamidopropyl Betaine, Decyl Glucoside, Cocamide DEA, Glycerin, Fragrance, Citric Acid, DMDM Hydantoin, Yellow 5, Red 4

Active Ingredient Purpose

Chloroxylenol 0.5% Antiseptic

Use:

For handwashing to decrease bacteria on the skin.

PACKAGE LABEL

Mission Linen Supply

Mission linen and uniform service

Antibacterial Foam Soap

Chloroxylenol 0.5%

High performance antibacterial foam soap

1 L (338 U.S. FL OZ)